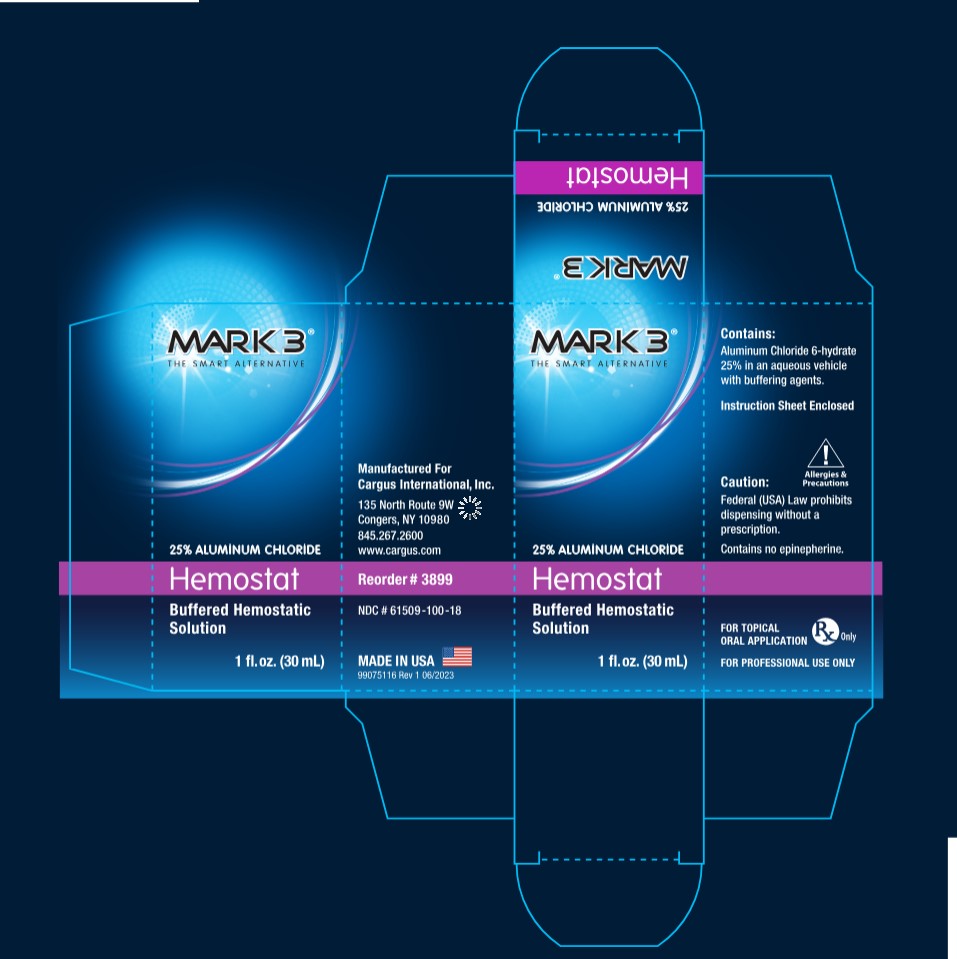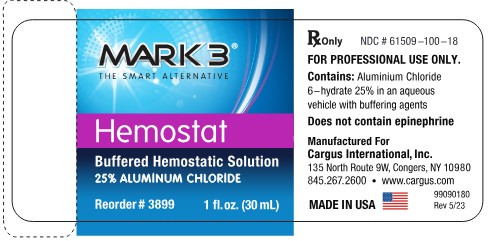 DRUG LABEL: Hemostat
NDC: 61509-100 | Form: SOLUTION
Manufacturer: Cargus International, Inc.
Category: prescription | Type: HUMAN PRESCRIPTION DRUG LABEL
Date: 20240509

ACTIVE INGREDIENTS: ALUMINUM CHLORIDE 7500 mg/30 mL
INACTIVE INGREDIENTS: WATER; PROPYLENE GLYCOL; POTASSIUM CHLORIDE; DMDM HYDANTOIN

DESCRIPTION:

Hemostat is a topical astringent solution of Aluminum Chloride. Gingival retraction can be achieved using a plain gingival retraction cord moistened with Hemostat solution.

PRECAUTIONS:

Discontinue use if irritation appears. For topical application only. Avoid eye contact.

BENEFITS:

Hemostat stops gingival bleeding fast. If you should inadvertantly damage the gingival margin during tooth preparation or while placing a strip, band or a cerival matrix, moisten the area with Hemostat which will control and stop bleeding quickly. Hemostat contains no epinephrine. The use of vasoconstrictors for gingival retractions and bleeding is potentially dangerous and should be avoided. A plain gingival retraction cord can be dipped in Hemostat solution and then placed into the gingival sulcus for its hemostatic action.

DIRECTIONS:

Soak a cotton tipped applicator with Hemostat. Apply to bleeding area with pressure until bleeding is stopped. Should a small dark coagulum appear, flush it away with water. This will have no effect on hemostatic action. Remove the impregnated cord from sulcus. Flush with water and dry with air. If hemostasis is not achieved, repeat application, rinse with water and air dry until bleeding is no longer present.

CONTRAINDICATIONS:

Do not use in patients with a known history of hyper sensitivity to aluminum chloride.

CAUTION:

Keep out of reach of children.

FOR PROFESSIONAL USE ONLY.